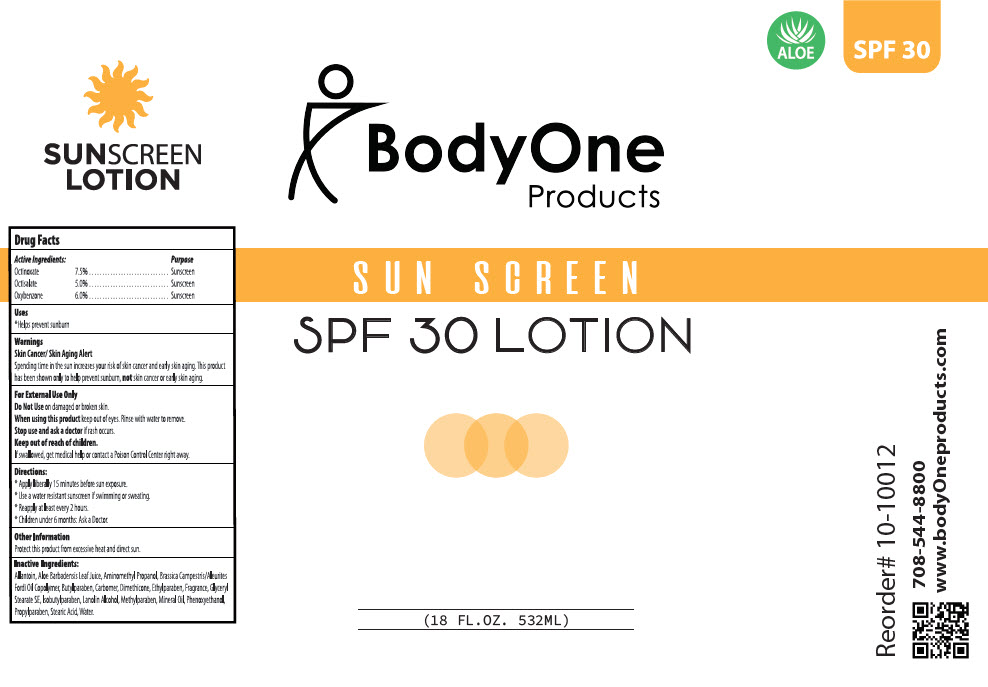 DRUG LABEL: Sunscreen with Aloe Vera SPF 30
NDC: 73563-011 | Form: LOTION
Manufacturer: Body One Products, Inc.
Category: otc | Type: HUMAN OTC DRUG LABEL
Date: 20200131

ACTIVE INGREDIENTS: Octinoxate 75 mg/1 mL; Octisalate 50 mg/1 mL; Oxybenzone 60 mg/1 mL
INACTIVE INGREDIENTS: Water; Allantoin; Carbomer Homopolymer Type B (Allyl Sucrose Crosslinked); GULOSE, L-; Mineral Oil; HEXAMETHYLDISILOXANE; AMINOMETHYLPROPANOL; Stearic Acid; Aloe vera leaf; Phenoxyethanol; Glyceryl Stearate SE; Cetostearyl alcohol; Polysorbate 60

Sunscreen with Aloe Vera SPF 30

Drug Facts

ACTIVE INGREDIENT

Active Ingredients | Purpose
Octinoxate 7.5% | Sunscreen
Octisalate 5.0% | Sunscreen
Oxybenzone 6.0% | Sunscreen

Uses

- Helps prevent sunburn

Warnings

Skin Cancer/Skin Aging Alert

Spending time in the sun increases your risk of skin cancer and early skin aging. This product has been shown only to help prevent sunburn, not skin cancer or early skin aging.

For external use only

Do Not Use on damaged skin or broken skin.

When using this product keep out of eyes. Rinse with water to remove.

Stop use and ask a doctor if rash occurs.

Keep out of reach of children.

If swallowed , get medical help or contact a Poison Control Center right away.

Directions

- Apply liberally 15 minutes before sun exposure.
- Use a water resistant sunscreen if swimming or sweating.
- Reapply at least every 2 hours.
- Children under 6 months: ask a Doctor.

Other Information

Protect this product container from excessive heat and direct sun.

Inactive Ingredients

Aloe Barbadensis Leaf Juice, Aminomethyl Propanol, Brassica Campestris/Aleurites Fordi Oil Copolymer, Butyl Paraben, Carbomer, Dimethicone, Ethylparaben, Fragrance,Glyceryl Stearate SE, Isobutylparaben, Lanolin Alcohol, Methylparaben,Mineral Oil, Phenoxyethanol, Propylparaben, Stearic Acid , Water.

Questions or Comments?

Call 1-800-544-8800

PRINCIPAL DISPLAY PANEL - 532 ML Bottle Label

BodyOne
Products

SUN SCREEN

SPF 30 LOTION

(18 FL.OZ. 532ML)